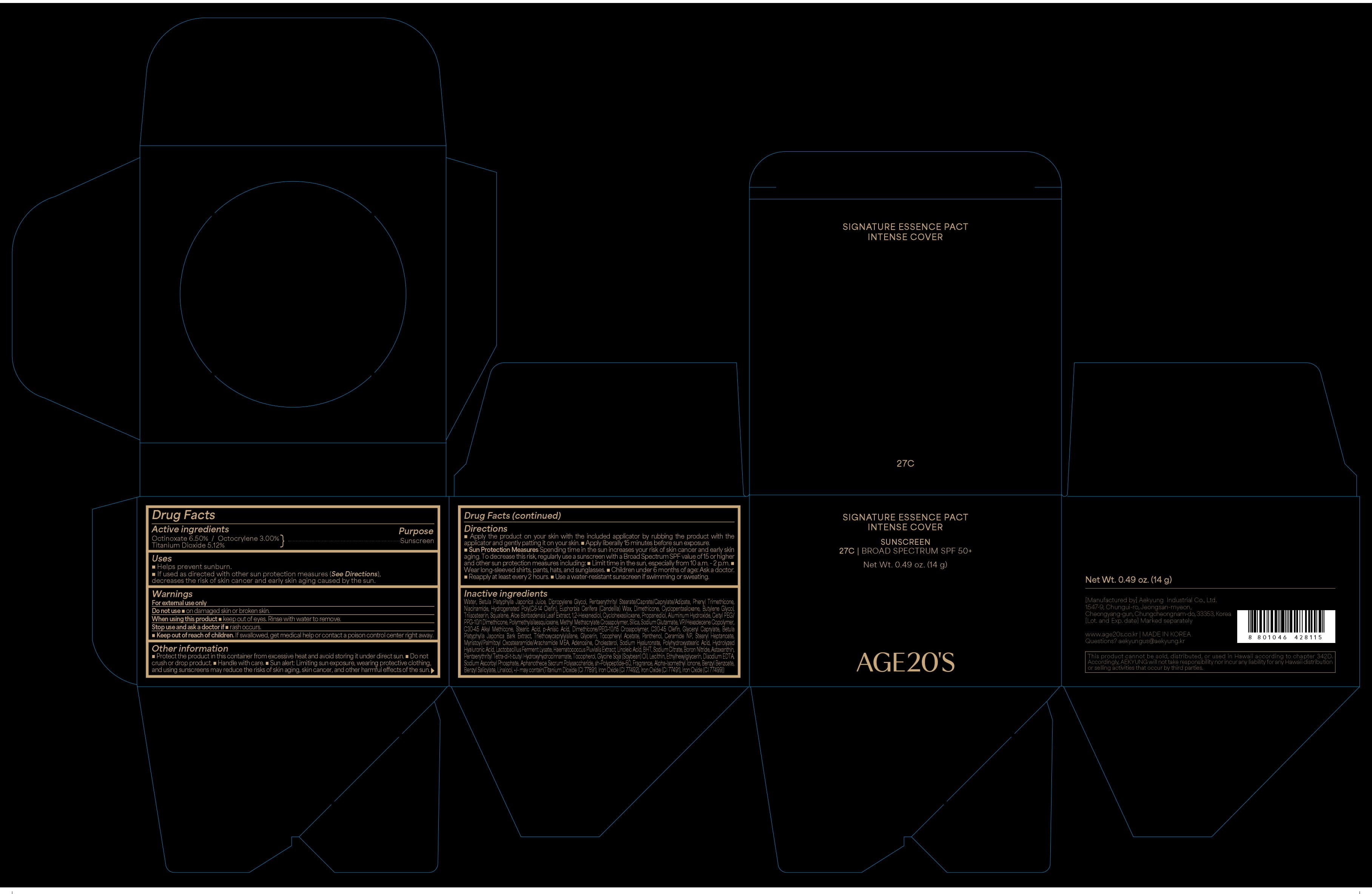 DRUG LABEL: AGE20S SIGNATURE ESSENCE PACT INTENSE COVER 27C
NDC: 67225-5127 | Form: CREAM
Manufacturer: Aekyung Industrial Co., Ltd.
Category: otc | Type: HUMAN OTC DRUG LABEL
Date: 20251209

ACTIVE INGREDIENTS: TITANIUM DIOXIDE 0.7168 g/14 g; OCTOCRYLENE 0.42 g/14 g; OCTINOXATE 0.91 g/14 g
INACTIVE INGREDIENTS: POLYMETHYLSILSESQUIOXANE (11 MICRONS); HYDROGENATED POLY(C6-14 OLEFIN; 2 CST); ALOE VERA LEAF; STEARIC ACID; P-ANISIC ACID; FERROSOFERRIC OXIDE; 1,2-HEXANEDIOL; ADENOSINE; PENTAERYTHRITYL STEARATE; PHENYL TRIMETHICONE; CERAMIDE NP; HYALURONATE SODIUM; ETHYLHEXYLGLYCERIN; C30-45 OLEFIN; TRIISOSTEARIN; MONOSODIUM GLUTAMATE; BUTYLATED HYDROXYTOLUENE; STEARYL HEPTANOATE; CYCLOMETHICONE 5; CYCLOMETHICONE 6; SODIUM ASCORBYL PHOSPHATE; FERRIC OXIDE YELLOW; ALUMINUM HYDROXIDE; HYDROGENATED SOYBEAN LECITHIN; DIPROPYLENE GLYCOL; WATER; POLYHYDROXYSTEARIC ACID STEARATE; LINOLEIC ACID; NIACINAMIDE; HYALURONIC ACID; CHOLESTEROL; PROPANEDIOL; FERRIC OXIDE RED; EDETATE DISODIUM; VINYLPYRROLIDONE/HEXADECENE COPOLYMER; C30-45 ALKYL METHICONE; BETULA PLATYPHYLLA RESIN; CANDELILLA WAX; SQUALANE; GLYCERIN; TRIETHOXYCAPRYLYLSILANE; PANTHENOL; TOCOPHEROL; CETYL PEG/PPG-10/1 DIMETHICONE (HLB 2); DIMETHICONE; BUTYLENE GLYCOL; DIMETHICONE/PEG-10/15 CROSSPOLYMER; GLYCERYL CAPRYLATE; ALPHA-TOCOPHEROL ACETATE; MYRISTOYL/PALMITOYL OXOSTEARAMIDE/ARACHAMIDE MEA; SODIUM CITRATE; BORON NITRIDE; SOYBEAN OIL

67225-5127 AGE20S SIGNATURE ESSENCE PACT INTENSE COVER 27C

ACTIVE INGREDIENT

Octinoxate 6.50 %

Titanium Dioxide 5.12 %

Octocrylene 3.00 %

PURPOSE

Sunscreen

INDICATIONS AND USAGE

■ Helps prevent sunburn.
■ If used as directed with other sun protection measures (See Directions), decreases the risk of skin cancer and early skin aging caused by the sun.

WARNINGS

For external use only

DO NOT USE

■ damaged skin or broken skin.

WHEN USING

this product ■ keep out of eyes. Rinse with water to remove.

STOP USE

and ask a doctor ■ rash occurs.

KEEP OUT OF REACH OF CHILDREN

If swallowed, get medical help or contact poison control center right away.

OTHER SAFETY INFORMATION

■ Protect the product in this container from excessive heat and avoid storing it under direct sun. ■ Do not crush or drop product.■ Handle with care.■ Sun alert: Limiting sun exposure, wearing protective clothing, and using sunscreens may reduce the risks of skin aging, skin cancer, and other harmful effects of the sun.

Directions
■ Apply the product on your skin with the included applicator by rubbing the product with the applicator and gently patting it on your skin.■ Apply liberally 15 minutes before sun exposure.
■ Sun Protection Measures Spending time in the sun increases your risk of skin cancer and early skin aging. To decrease this risk, regularly use a sunscreen with a Broad Spectrum SPF value of 15 or higher and other sun protection measures including:■ Limit time in the sun, especially from 10a.m. - 2 p.m. ■ Wear long-sleeved shirts, pants, hats, and sunglasses.■ Children under 6 months of age: Ask a doctor. ■Reapply at least every 2 hours.■ Use a water-resistant sunscreen if swimming or sweating.

INACTIVE INGREDIENT

Water, Betula Platyphylla Japonica Juice, Dipropylene Glycol, Pentaerythrityl Stearate/Caprate/Caprylate/Adipate, Phenyl Trimethicone, Polymethylsilsesquioxane, Hydrogenated Poly(C6-14 Olefin), Niacinamide, Euphorbia Cerifera (Candelilla) Wax, Dimethicone, Cyclopentasiloxane, Butylene Glycol, Aloe Barbadensis Leaf Extract, Squalane, Triisostearin, 1,2-Hexanediol, Cyclohexasiloxane, Propanediol, Cetyl PEG/PPG-10/1 Dimethicone, Aluminum Hydroxide, Sodium Glutamate, VP/Hexadecene Copolymer, C30-45 Alkyl Methicone, Stearic Acid, p-Anisic Acid, Dimethicone/PEG-10/15 Crosspolymer, C30-45 Olefin, Glyceryl Caprylate, Betula Platyphylla Japonica Bark Extract, Glycerin, Fragrance, Triethoxycaprylylsilane, Panthenol, Tocopheryl Acetate, Ceramide NP, Stearyl Heptanoate, Adenosine, Myristoyl/Palmitoyl Oxostearamide/Arachamide MEA, Cholesterol, Hydrolyzed Hyaluronic Acid, Polyhydroxystearic Acid, Sodium Hyaluronate, Lactobacillus Ferment Lysate, Linoleic Acid, BHT, Sodium Citrate, Boron Nitride, Tocopherol, Aphanothece Sacrum Polysaccharide, Glycine Soja (Soybean) Oil, Ethylhexylglycerin, Lecithin, Disodium EDTA, Sodium Ascorbyl Phosphate, sh-Polypeptide-60, Alpha-Isomethyl Ionone, Benzyl Benzoate, Benzyl Salicylate, Linalool, +/- may contain (Titanium Dioxide (CI 77891), Iron Oxide (CI 77491), Iron Oxide (CI 77492), Iron Oxide (CI 77499))